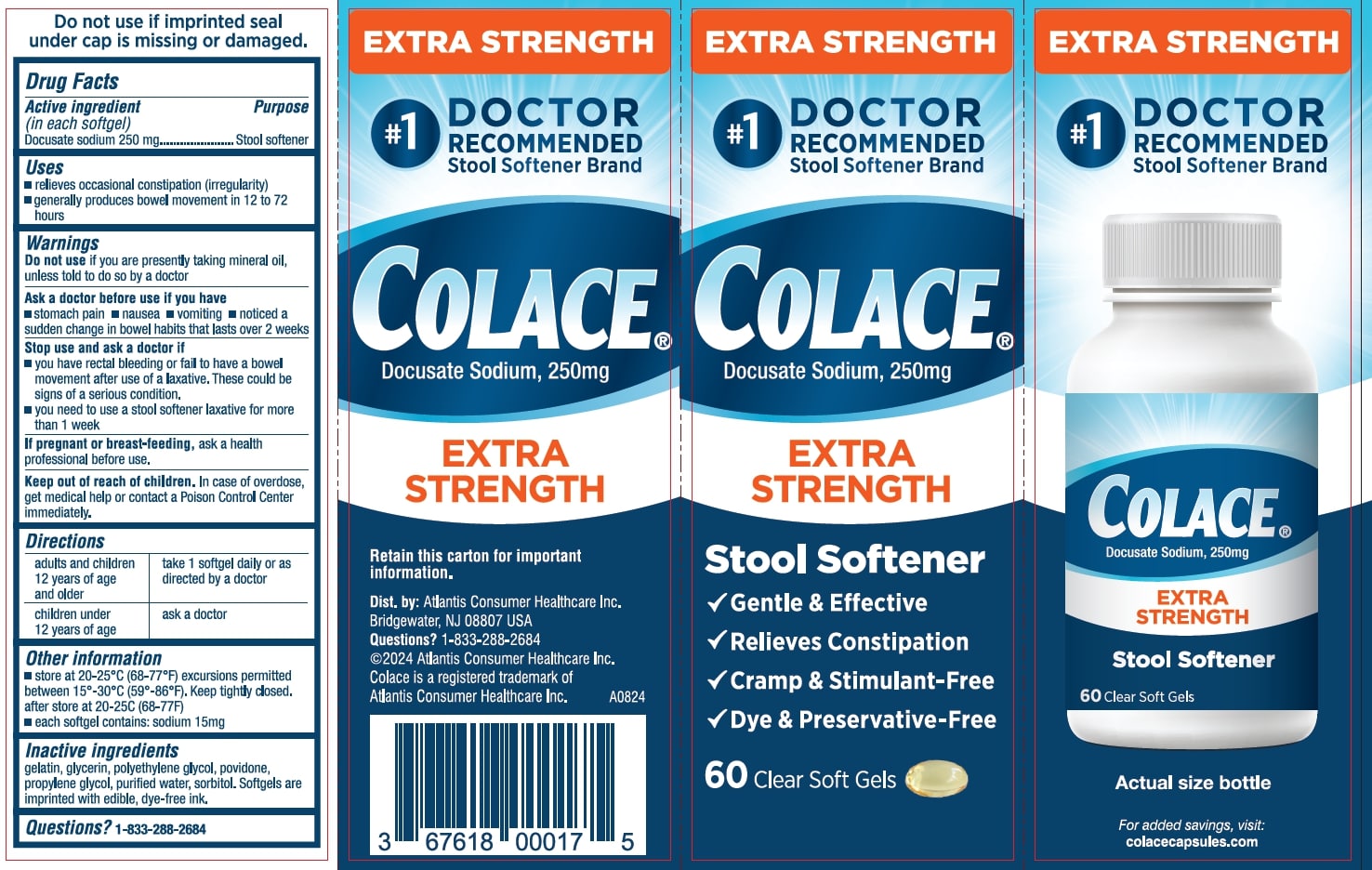 DRUG LABEL: COLACE EXTRA STRENGTH
NDC: 67618-201 | Form: CAPSULE, LIQUID FILLED
Manufacturer: Atlantis Consumer Healthcare Inc.
Category: otc | Type: HUMAN OTC DRUG LABEL
Date: 20250501

ACTIVE INGREDIENTS: DOCUSATE SODIUM 250 mg/1 1
INACTIVE INGREDIENTS: GELATIN, UNSPECIFIED; GLYCERIN; POLYETHYLENE GLYCOL, UNSPECIFIED; CROSPOVIDONE (120 .MU.M); PROPYLENE GLYCOL; WATER; SORBITOL

Docusate Sodium - Stool Softener Laxative

Active ingredient (in each softgel)

Docusate Sodium 250 mg

Purpose

Stool softener

Uses

- relieves occasional constipation (irregularity)
  • generally produces a bowel movement within 12 to 72 hours.

Warnings

Do not useif you are presently taking mineral oil, unless told to do so by a doctor.

Ask a doctor before use if you have

- Stomach pain
- Nausea
- Vomiting
- Noticed a sudden change in bowel habits that lasts over 2 weeks

Stop use and ask a doctor if

- you have rectal bleeding or fail to have a bowel movement after use of a laxative.
  These can be signs of a serious condition
- you need to use a stool softner laxative for more than 1 week

If pregnant or breast-feeding, ask a health care professional before use.

Keep out of reach of children

If swallowed, get medical help or contact a Poison Control Center immediately.

Directions

adults and children 12 years of age and older | take 1 softgel daily or as directed by a doctor.
children under 12 years of age | ask a doctor

Other information

- each softgel contains:sodium 15mg
- store at 20-25°C (68-77°F).
- Keep carton for full product information

Inactive ingredients

gelatin, glycerin, polyethylene glycol, povidone, propylene glycol, purified water, sorbitol. Softgels are imprinted with edible, dye-free ink.

Questions?

1-833-288-2684

Principal Display Panel

EXTRA STRENGTH

#1 DOCTOR RECOMMENDED

Stool Softner Brand

COLACE

Docusate Sodium, 250mg

EXTRA STRENGTH

Stool Softner

√Gentle & Effective

√Relieves Constipation

√Cramp & Stimulant-Free

√Dye & Preservative-Free √

60 Clear Soft Gels

Retain this carton for important information.

Dis. By: Atlantis Consumer Healthcare Inc.

Bridgewater, NJ 08807 USA

Questions? 1-833-288-2684

©2024 Atlantis Consumer Healthcare Inc.

Colace is a registered trademark of Atlantis Consumer Healthcare Inc.

A0824